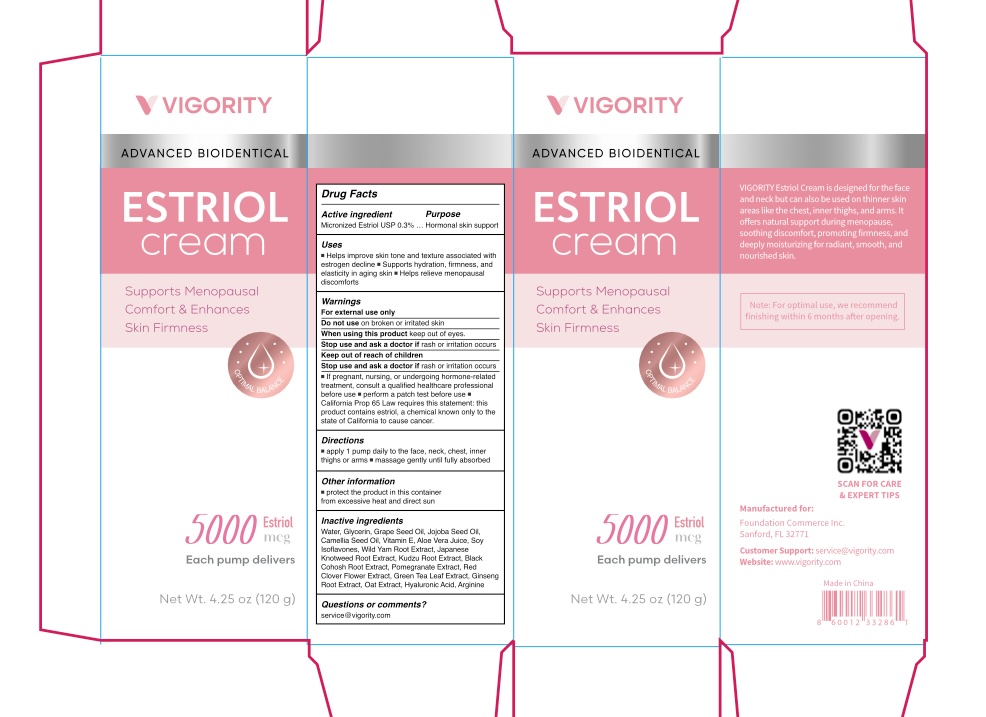 DRUG LABEL: Vigority Estriol Cream
NDC: 85739-003 | Form: CREAM
Manufacturer: FOUNDATION COMMERCE INC
Category: otc | Type: HUMAN OTC DRUG LABEL
Date: 20250730

ACTIVE INGREDIENTS: ESTRIOL 3 mg/1 g
INACTIVE INGREDIENTS: GLYCERIN; PUERARIA MONTANA VAR. LOBATA ROOT; CAMELLIA OIL; GRAPE SEED OIL; POMEGRANATE SEED OIL; GREEN TEA LEAF; HYALURONIC ACID; ARGININE; TOCOPHEROL; JOJOBA OIL; BLACK COHOSH; DIOSCOREA OPPOSITIFOLIA (WILD YAM) ROOT; ALOE VERA LEAF JUICE; REYNOUTRIA JAPONICA ROOT; RED CLOVER; AVENA SATIVA WHOLE; PANAX GINSENG ROOT; WATER; SOY ISOFLAVONES

Initial Drug Listing - Vigority Estriol Cream

ACTIVE INGREDIENT

Micronized Estriol USP 0.3%

PURPOSE

Hormonal Skin Support

INDICATIONS AND USAGE

- Helps improve skin tone and texture associated with estrogen decline
- Supports hydration, firmness, and elasticity in aging skin
- Helps relieve menopausal discomforts

WARNINGS

For external use only

DO NOT USE

on broken or irritated skin

WHEN USING

keep out of eyes.

STOP USE

if rash or irritation occurs

ASK DOCTOR

If pregnant, nursing, or undergoing hormone-related treatment, consult a qualified healthcare professional before use.

Keep out of reach of children

DOSAGE AND ADMINISTRATION

- apply 1 pump daily to the face, neck, chest, inner thighs or arms
- message gently until fully absorbed

OTHER SAFETY INFORMATION

Protect the product in this container from excessive heat and direct sun.

INACTIVE INGREDIENT

Water, Glycerin, Grape Seed Oil, Jojoba Seed Oil, Camellia Seed Oil, Vitamin E, Aloe Vera Juice, Soy Isoflavones, Wild Yam Root Extract, Japanese Knotweed Root Extract, Kudzu Root Extract, Black Cohosh Root Extract, Pomegranate Extract, Red Clover Flower Extract, Green Tea Leaf Extract, Ginseng Root Extract, Oat Extract, Hyaluronic Acid, Arginine

QUESTIONS

service@vigority.com